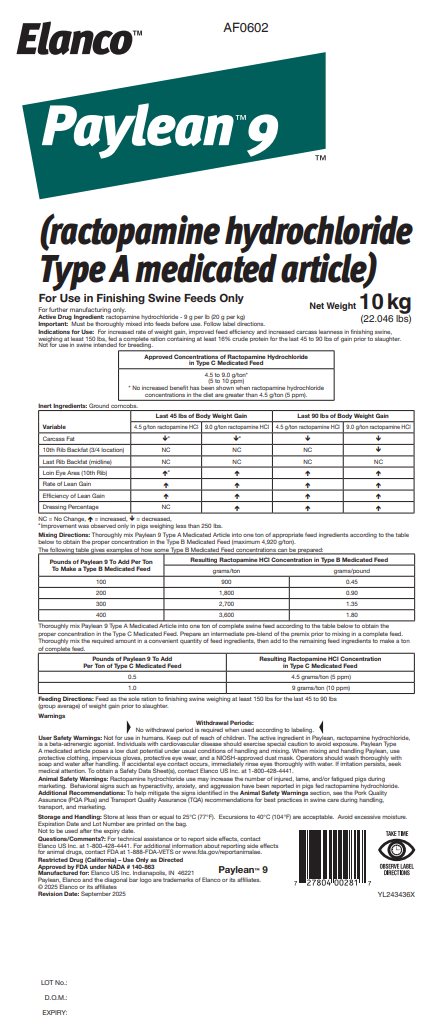 DRUG LABEL: Paylean 9
NDC: 58198-0602 | Form: GRANULE
Manufacturer: Elanco US Inc.
Category: animal | Type: VFD TYPE A MEDICATED ARTICLE ANIMAL DRUG LABEL
Date: 20251216

ACTIVE INGREDIENTS: ractopamine hydrochloride 20 g/1 kg

Elanco™

AF0602

Paylean™9

(ractopamine hydrochloride
Type A medicated article)

For Use in Finishing Swine Feeds Only

For further manufacturing only.

Net Weight 10 kg
(22.046 lbs)

Active Drug Ingredient: ractopamine hydrochloride - 9 g per lb (20 g per kg)

Important: Must be thoroughly mixed into feeds before use. Follow label directions.

INDICATIONS AND USAGE

Indications for Use: For increased rate of weight gain, improved feed efficiency and increased carcass leanness in finishing swine, weighing at least 150 lbs, fed a complete ration containing at least 16% crude protein for the last 45 to 90 lbs of gain prior to slaughter.

Not for use in swine intended for breeding.

Appropriate Concentration of Ractopamine Hydrochloride
in Type C Medicated Feed

4.5 to 9.0 g/ton*

(5 to 10 ppm)

* No increased benefit has been shown when ractopamine hydrochloride concentrations in the diet are greater than 4.5 g/ton (5 ppm).

Inert Ingredients: Ground corncobs.

 | Last 45 lbs of Body Weight Gain |  | Last 90 lbs of Body Weight Gain
Variable | 4.5 g/ton ractopamine HCl | 9.0 g/ton ractopamine HCl | 4.5 g/ton ractopamine HCl | 9.0 g/ton ractopamine HCl
Carcass Fat | ↓a | ↓a | ↓ | ↓
10th Rib Backfat (3/4 location) | NC | NC | NC | ↓
Last Rib Backfat (midline) | NC | NC | NC | NC
Loin Eye Area (10th Rib) | ↑a | ↑ | ↑ | ↑
Rate of Lean Gain | ↑ | ↑ | ↑ | ↑
Efficiency of Lean Gain | ↑ | ↑ | ↑ | ↑
Dressing Percentage | NC | ↑ | ↑ | ↑
NC = No Change, ↑ = increased, ↓ = decreased,
a Improvement was observed only in pigs weighing less than 250 lbs.

DOSAGE AND ADMINISTRATION

Mixing Directions: Thoroughly mix Paylean 9 Type A Medicated Article into one ton of appropriate feed ingredients according to the table below to obtain the proper concentration in the Type B Medicated Feed (maximum 4,920 g/ton).
The following table gives examples of how some Type B Medicated Feed concentrations can be prepared:

Pounds of Paylean 9 To Add Per Ton To Make a Type B Medicated Feed | Resulting Ractopamine HCl Concentration in Type B Medicated Feed
Pounds of Paylean 9 To Add Per Ton To Make a Type B Medicated Feed | grams/ton | grams/pound
100 | 900 | 0.45
200 | 1,800 | 0.90
300 | 2,700 | 1.35
400 | 3,600 | 1.80

Thoroughly mix Paylean 9 Type A Medicated Article into one ton of complete swine feed according to the table below to obtain the proper concentration in the Type C Medicated Feed. Prepare an intermediate pre-blend of the premix prior to mixing in a complete feed. Thoroughly mix the required amount in a convenient quantity of feed ingredients, then add to the remaining feed ingredients to make a ton of complete feed.

Pounds of Paylean 9 To Add Per Ton of Type C Medicated Feed | Resulting Ractopamine HCl Concentration in Type C Medicated Feed
0.5 | 4.5 grams/ton (5 ppm)
1.0 | 9 grams/ton (10 ppm)

Feeding Directions: Feed as the sole ration to finishing swine weighing at least 150 lbs for the last 45 to 90 lbs (group average) of weight gain prior to slaughter.

Warnings

Withdrawal Periods:

No withdrawal period is required when used according to labeling.

User Safety Warnings: Not for use in humans. Keep out of reach of children. The active ingredient in Paylean, ractopamine hydrochloride, is a beta-adrenergic agonist. Individuals with cardiovascular disease should exercise special caution to avoid exposure. Paylean Type A medicated article poses a low dust potential under usual conditions of handling and mixing. When mixing and handling Paylean, use protective clothing, impervious gloves, protective eye wear, and a NIOSH-approved dust mask. Operators should wash thoroughly with soap and water after handling. If accidental eye contact occurs, immediately rinse eyes thoroughly with water. If irritation persists, seek medical attention. To obtain a Safety Data Sheet(s), contact Elanco US Inc. at 1-800-428-4441.

Animal Safety Warnings: Ractopamine hydrochloride use may increase the number of injured, lame, and/or fatigued pigs during marketing. Behavioral signs such as hyperactivity, anxiety, and aggression have been reported in pigs fed ractopamine hydrochloride.

Additional Recommendations: To help mitigate the signs identified in the Animal Safety Warnings section, see the Pork Quality Assurance (PQA Plus) and Transport Quality Assurance (TQA) recommendations for best practices in swine care during handling, transport, and marketing.

Storage and Handling: Store at less than or equal to 25°C (77°F). Excursions to 40°C (104°F) are acceptable. Avoid excessive moisture.

Expiration Date and Lot Number are printed on the bag.

Not to be used after the expiry date.

Questions/Comments?: For technical assistance or to report side effects, contact Elanco US Inc. at 1-800-428-4441. For additional information about reporting side effects for animal drugs, contact FDA at 1-888-FDA-VETS or www.fda.gov/reportamimalae.

Restricted Drug (California) - Use Only as Directed

Approved by FDA under NADA # 140-863

Manufactured for: Elanco US Inc. Indianapolis, IN 46221 Paylean™ 9

Paylean, Elanco and the diagonal bar logo are trademarks of Elanco or its affiliates.

© 2025 Elanco or its affiliates

Revision Date: September 2025

TAKE TIME
OBSERVE LABEL
DIRECTIONS

YL243436X

LOT No.:

D.O.M.:

EXPIRY:

Principal Display Panel – 10 kg Bag Label

Elanco™

AF0602

Paylean™9

(ractopamine hydrochloride
Type A medicated article)

For Use in Finishing Swine Feeds Only

For further manufacturing only.

Net Weight 10 kg
(22.046 lbs)